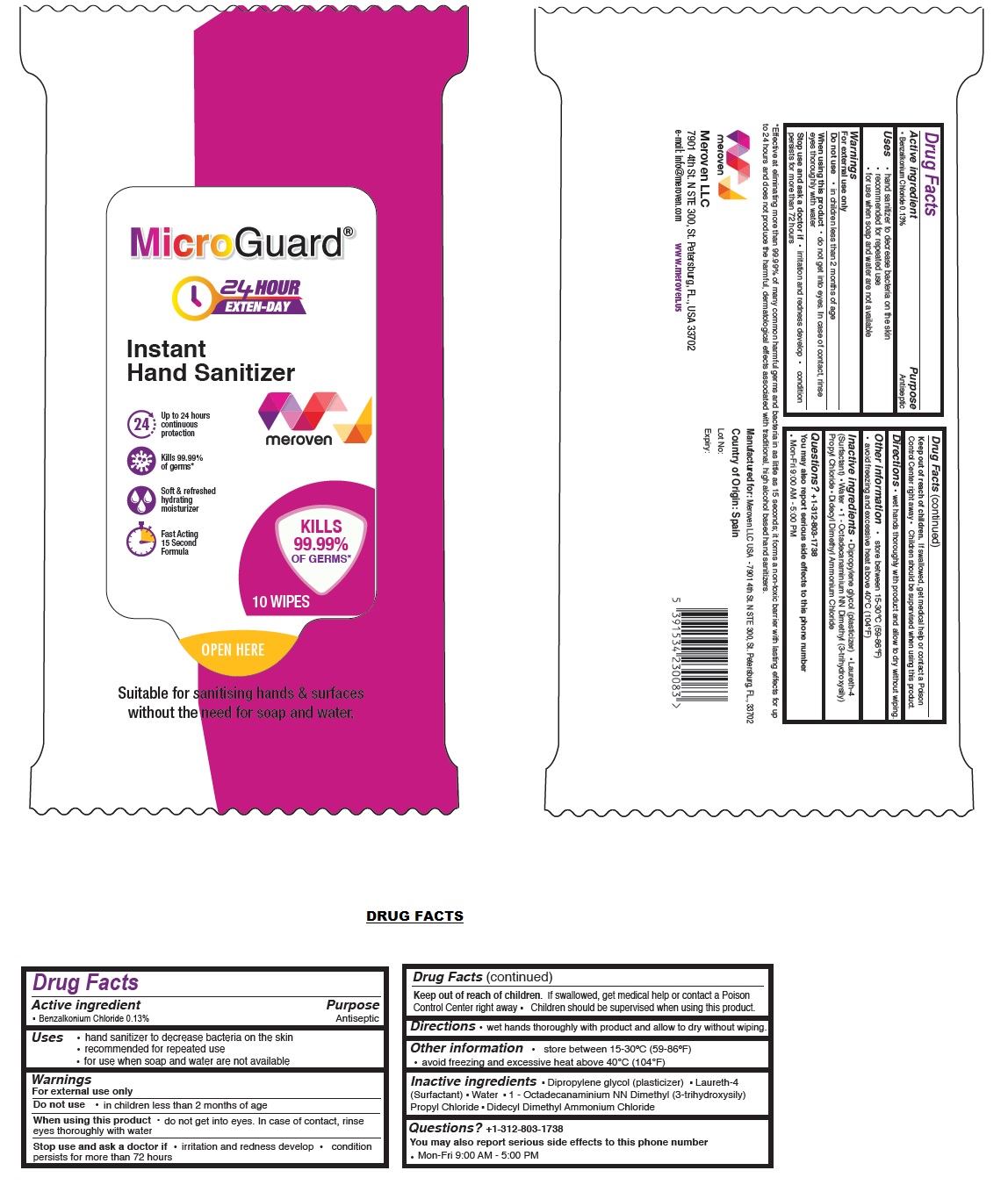 DRUG LABEL: Micro Guard 24 Hours Instant Hand Sanitizer Wipes
NDC: 74653-301 | Form: CLOTH
Manufacturer: Meroven LLC
Category: otc | Type: HUMAN OTC DRUG LABEL
Date: 20200601

ACTIVE INGREDIENTS: BENZALKONIUM CHLORIDE 1.3 mg/1 mL
INACTIVE INGREDIENTS: DIPROPYLENE GLYCOL; LAURETH-4; WATER; OCTADECYLDIMETHYL(3-TRIHYDROXYSILYLPROPYL)AMMONIUM CHLORIDE; DIDECYLDIMONIUM CHLORIDE

MicroGuard® Instant Hand Sanitizer Wipes

Active ingredient

▪ Benzalkonium Chloride 0.13%

Purpose

Antiseptic

INDICATIONS AND USAGE

Uses ▪ hand sanitizer to decrease bacteria on the skin

▪ recommended for repeated use

▪ for use when soap and water are not available

Warnings

For external use only

Do not use▪ in children less than 2 months of age

When using this product ▪ do not get into eyes. In case of contact, rinse eyes thoroughly with water

Stop use and ask a doctor if ▪ irritation and redness develop ▪ condition persists for more than 72 hours

Keep out of reach of children. If swallowed, get medical help or contact a Poison Control Center right away ▪ Children should be supervised when using this product.

DOSAGE AND ADMINISTRATION

Directions ▪ wet hands thoroughly with product and allow to dry without wiping.

Other information ▪ store between 15-30°C (59-86°F)

▪ avoid freezing and excessive heat above 40°C (104°F)

INACTIVE INGREDIENT

Inactive ingredients ▪ Dipropylene glycol (plasticizer) ▪ Laureth-4 (Surfactant) ▪ Water ▪ 1 - Octadecanaminium NN

Dimethyl (3-trihydroxysily) Propyl Cloride ▪ Didecyl Dimethyl Ammonium Chloride

Questions? +1-312-803-1738

You may also report serious side effects to this phone number.

Mon-Fri 9:00 AM - 5:00 PM

EXTEN-DAY

24 HOUR

Up to 24 hours continuous protection

Kills 99.99% of germs*

Soft & refreshed hydrating moisturizer

Fast Acting 15 Second Formula

Suitable for sanitising hands & surfaces without the need for soap and water.

*Effective at eliminating more than 99.99% of many common harmful germs and bacteria in as little as 15 seconds; it forms a non-toxic barrier with lasting effects for up to 24 hours and does not produce the harmful, dermatological effects associated with traditional, high alcohol based hand sanitizers.

Manufactured for: Meroven LLC - 7901 4th St. N STE 300,St.Petersburg, FL., 33702

Country of origin: Spain